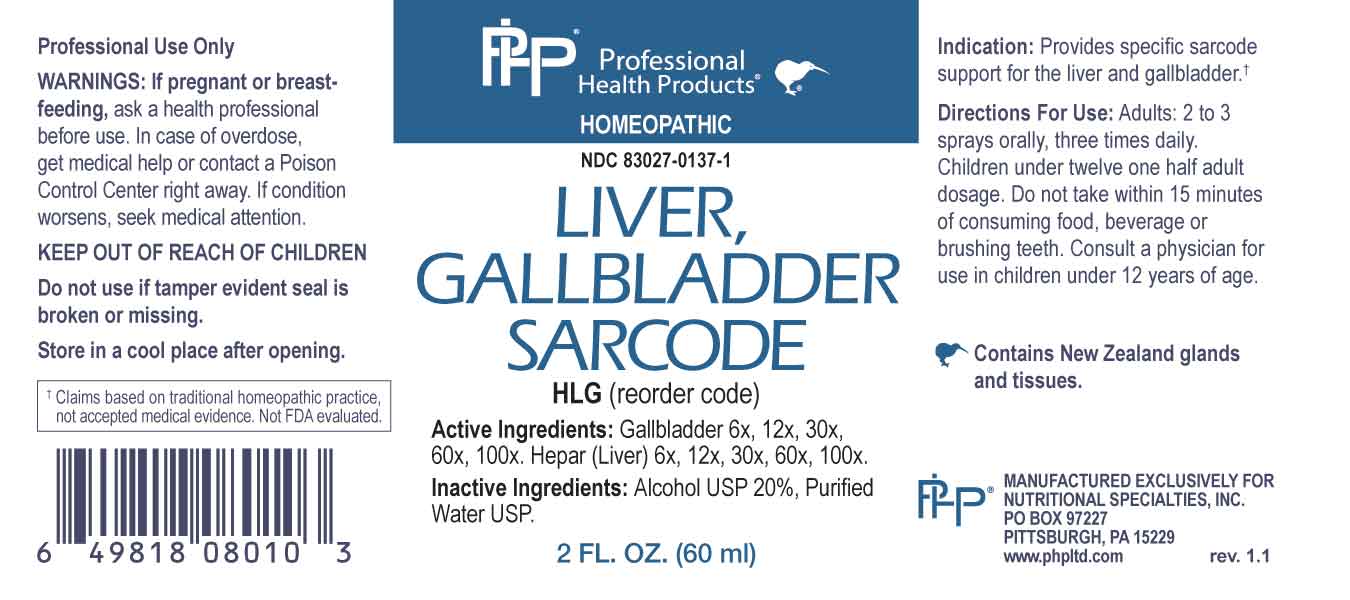 DRUG LABEL: Liver, Gallbladder Sarcode
NDC: 83027-0137 | Form: SPRAY
Manufacturer: Nutritional Specialties, Inc.
Category: homeopathic | Type: HUMAN OTC DRUG LABEL
Date: 20240524

ACTIVE INGREDIENTS: BOS TAURUS GALLBLADDER 6 [hp_X]/1 mL; BEEF LIVER 6 [hp_X]/1 mL
INACTIVE INGREDIENTS: WATER; ALCOHOL

DRUG FACTS:

ACTIVE INGREDIENTS:

Gallbladder 6X, 12X, 30X, 60X, 100X, Hepar (Liver) 6X, 12X, 30X, 60X, 100X.

PURPOSE:

Provides specific sarcode support for the liver and gallbladder.†

†Claims based on traditional homeopathic practice, not accepted medical evidence. Not FDA evaluated.

WARNINGS:

Professional Use Only

If pregnant or breast-feeding, ask a health professional before use.

In case of overdose, get medical help or contact a Poison Control Center right away.

If condition worsens, seek medical attention.

KEEP OUT OF REACH OF CHILDREN

Do not use if tamper evident seal is broken or missing.

Store in a cool place after opening

KEEP OUT OF REACH OF CHILDREN:

In case of overdose, get medical help or contact a Poison Control Center right away.

DIRECTIONS:

Adults: 2 to 3 sprays orally, three times daily. Children under twelve one half adult dosage. Do not take within 15 minutes of consuming food, beverage or brushing teeth. Consult a physician for use in children under 12 years of age.

INDICATIONS:

Provides specific sarcode support for the liver and gallbladder.†

†Claims based on traditional homeopathic practice, not accepted medical evidence. Not FDA evaluated.

INACTIVE INGREDIENTS:

Alcohol USP 20%, Purified Water USP.

QUESTIONS:

MANUFACTURED EXCLUSIVELY FOR

NUTRITIONAL SPECIALTIES, INC.

PO BOX 97227

PITTSBURG, PA 15229

www.phpltd.com

PACKAGE LABEL DISPLAY:

Professional

Health Products

HOMEOPATHIC

NDC 83027-0137-1

LIVER, GALLBLADDER

SARCODE

2 FL. OZ (60 ml)